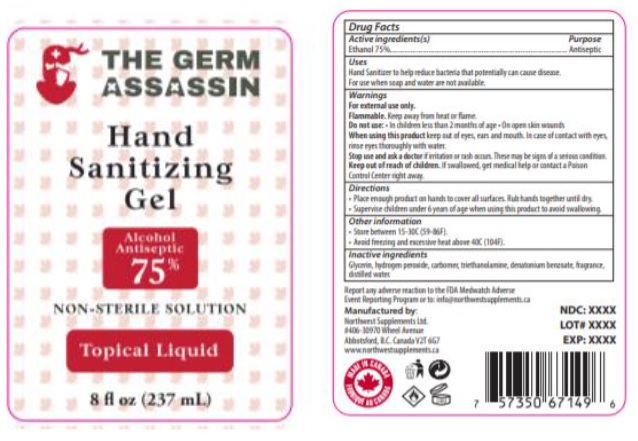 DRUG LABEL: The Germ Assassin
NDC: 80984-002 | Form: LIQUID
Manufacturer: Northwest Supplements Ltd.
Category: otc | Type: HUMAN OTC DRUG LABEL
Date: 20201102

ACTIVE INGREDIENTS: ALCOHOL 75 mL/100 mL
INACTIVE INGREDIENTS: GLYCERIN; HYDROGEN PEROXIDE; CARBOMER HOMOPOLYMER, UNSPECIFIED TYPE; TROLAMINE; DENATONIUM BENZOATE; WATER; MENTHA SPICATA OIL; LAVENDER OIL; TEA TREE OIL; EUCALYPTUS OIL; COCONUT OIL; ORANGE OIL; ALOE; .ALPHA.-TOCOPHEROL; EAST INDIAN LEMONGRASS OIL

The Germ Assassin

Active Ingredients

USP Alcohol 75%

Purpose

Antiseptic

Warning Section

- For external use only.
- Flammable. Keep away from heat or flame.

Do not use:

- In children less than 2 months of age
- On open skin wounds
- When using this product keep out of eyes, ears and mouth. In case of contact with eyes, rinse eyes thoroughly with water.
- Stop use and ask a doctor if irritation or rash occurs. These may be signs of a serious condition.
- Keep out of reach of children. If swallowed, get medical help or contact a Poison Control Center right away.

Uses

- Hand Sanitizer to help reduce bacteria that potentially can cause disease.
- For use when soap and water are not available.

Keep out of reach of children.

If swallowed, get medical help or contact a Poison Control Center right away.

Directions

• Place enough product on hands to cover all surfaces. Rub hands together until dry.
• Supervise children under 6 years of age when using this product to avoid swallowing.

Other information

• Store between 15-30C (59-86F).
• Avoid freezing and excessive heat above 40C (104F)

Inactive Ingredient

Glycerin, Hydrogen Peroxide, Carbomer, Triethanolamine, Denatonium Benzoate, Water, Fragrance